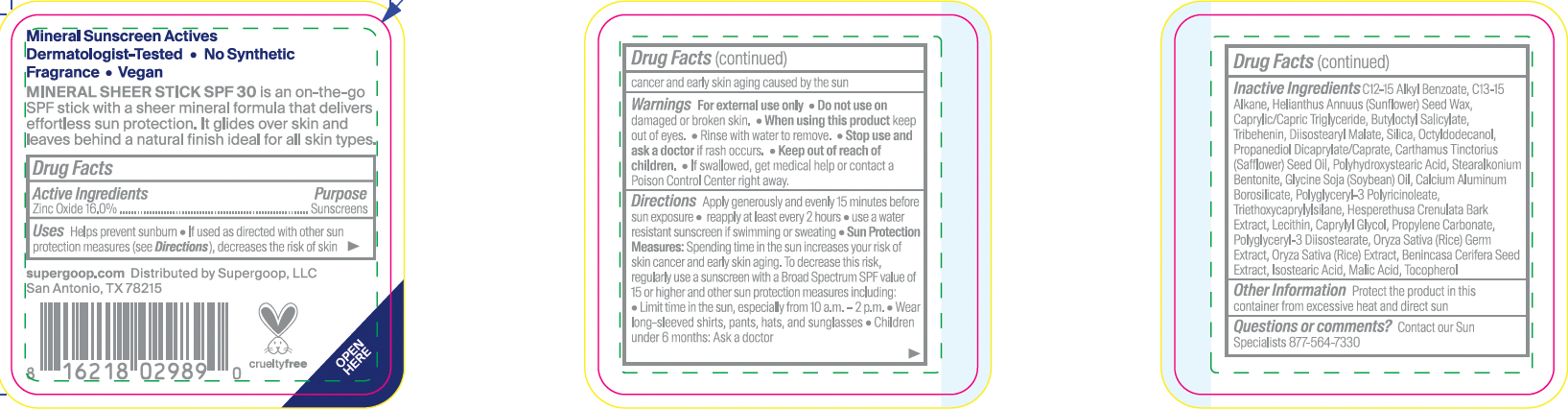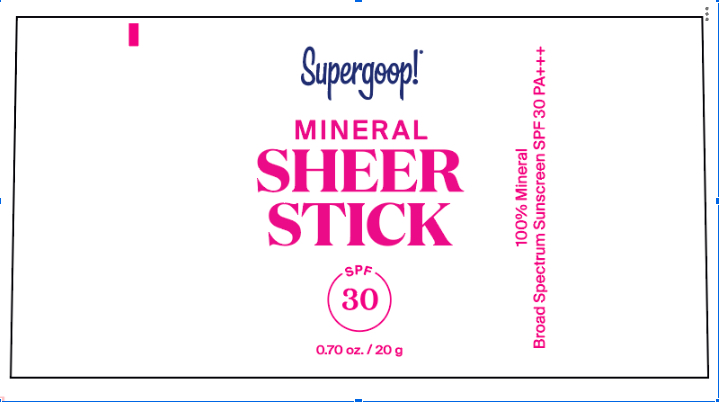 DRUG LABEL: Mineral Sheer Stick
NDC: 75936-637 | Form: STICK
Manufacturer: Supergoop, LLC
Category: otc | Type: HUMAN OTC DRUG LABEL
Date: 20251217

ACTIVE INGREDIENTS: ZINC OXIDE 16 g/100 g
INACTIVE INGREDIENTS: NARINGI CRENULATA WHOLE; HELIANTHUS ANNUUS SEED WAX; BUTYLOCTYL SALICYLATE; POLYHYDROXYSTEARIC ACID STEARATE; DISTEARYL METHYL BENZYL AMMONIUM CHLORIDE; ISOSTEARIC ACID; SAFFLOWER OIL; SOYBEAN OIL; POLYGLYCERYL-3 PENTARICINOLEATE; POLYGLYCERYL-3 DIISOSTEARATE; PROPYLENE CARBONATE; RICE GERM; MEDIUM-CHAIN TRIGLYCERIDES; C13-15 ALKANE; TRIBEHENIN; SILICON DIOXIDE; CALCIUM ALUMINUM BOROSILICATE; TRIETHOXYCAPRYLYLSILANE; OCTYLDODECANOL; PROPANEDIOL DICAPRYLATE/CAPRATE; DIISOSTEARYL MALATE; BENINCASA HISPIDA SEED; CAPRYLYL GLYCOL; ALKYL (C12-15) BENZOATE; LECITHIN, SOYBEAN

Mineral Sheer Stick SPF 30

Active Ingredients: Zinc Oxide 16.0%...Sunscreen

PURPOSE

Helps prevent sunburn

If used as directed with other sun protection measures (see Directions), decreases the risk of skin cancer and early skin aging caused by the sun

Keep out of reach of children. If product is swallowed, get medical help, or contact a poison control center right away.

WARNINGS

For External use only

Do not use on damaged or broken skin

When using this product, keep out of eyes. Rinse with water to remove

Stop use and ask a doctor if rash occurs

Directions

Apply generously and evenly 15 minutes before sun exposure

- Reapply at least every 2 hours
- use a water resistant sunscreen if swimming or sweating

Sun Protection Measures: Spending time in the sun increases your risk of skin cancer and early skin aging. To decrease this risk, regularly use a sunscreen with a Broad Spectrum SPF value of 15 or higher and other sun protection measures including:

- Limit time in the sun, especially from 10 a.m.- 2 p.m.
- Wear long-sleeved shirts, pants, hats, and sunglasses
- Children under 6 months: Ask a doctor

INACTIVE INGREDIENT

Inactive Ingredients: C12-15 Alkyl Benzoate, C13-15 Alkane, Helianthus Annuus (Sunflower) Seed Wax,Caprylic/Capric Triglyceride, Butyloctyl Salicylate, Tribehenin, Diisostearyl Malate, Silica,Octyldodecanol, Propanediol Dicaprylate/Caprate, Carthamus Tinctorius (Safflower)SeedOil, Polyhydroxystearic Acid, Stearalkonium Bentonite, Glycine Soja(Soybean) Oil, CalciumAluminum Borosilicate, Polyglyceryl-3 Polyricinoleate, Triethoxycaprylylsilane,Hesperethusa Crenulata Bark Extract, Lecithin, Caprylyl Glycol, Propylene Carbonate,Polyglyceryl-3 Diisostearate, Oryza Sativa (Rice) Germ Extract, Oryza Sativa (Rice) Extract,Benincasa Cerifera Seed Extract, Isostearic Acid, Malic Acid, Tocopherol

Questions or Comments? Contact out Sun Specialist 877-564-7330

PACKAGE LABEL

Mineral Sheer Stick SPF 30 (0.70 oz. / 20 g)